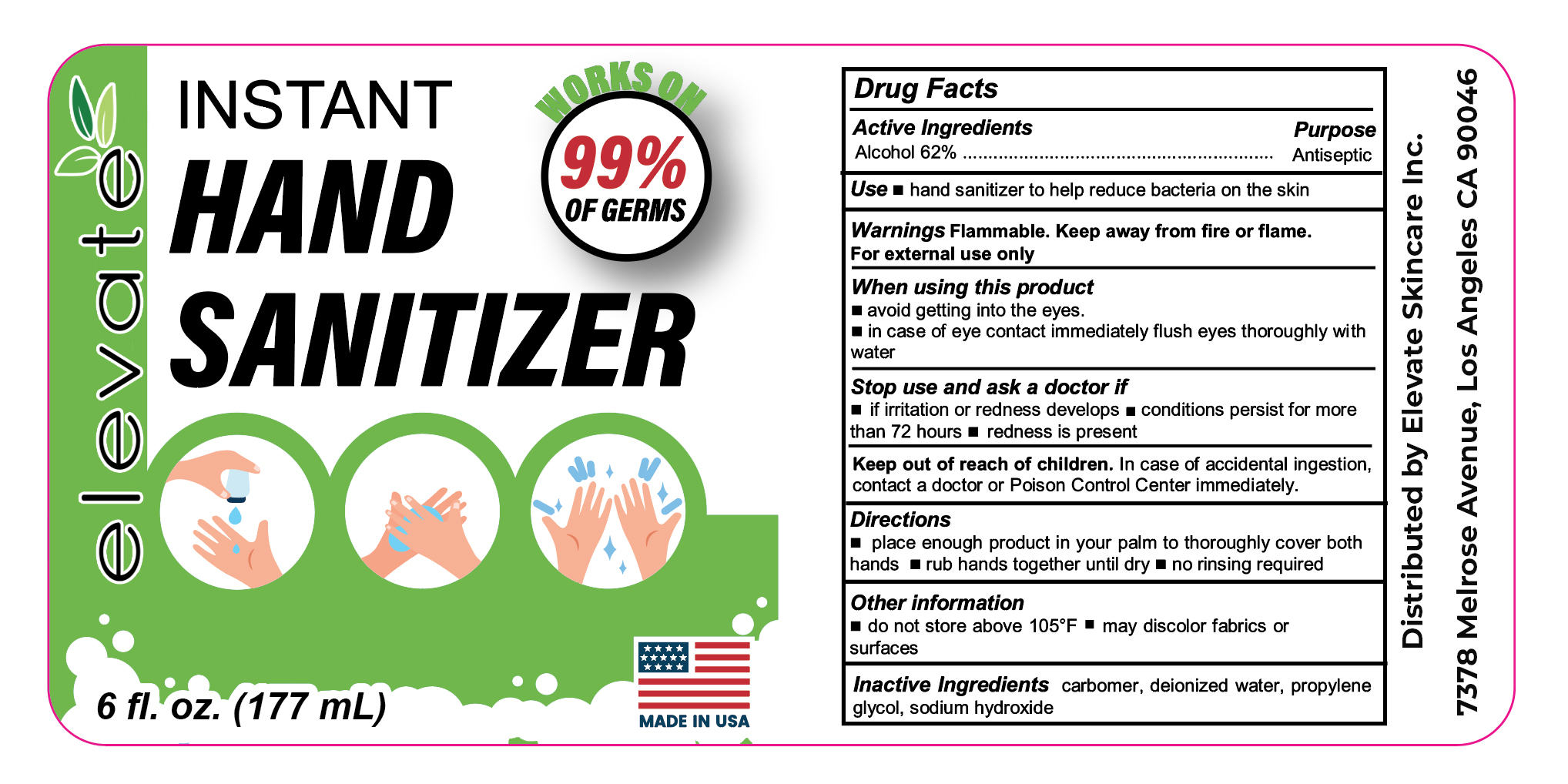 DRUG LABEL: Hand Sanitizer
NDC: 74175-001 | Form: LIQUID
Manufacturer: Elevate Skincare, Inc.
Category: otc | Type: HUMAN OTC DRUG LABEL
Date: 20200410

ACTIVE INGREDIENTS: ALCOHOL 62 mL/100 mL
INACTIVE INGREDIENTS: PROPYLENE GLYCOL; WATER; CARBOMER HOMOPOLYMER, UNSPECIFIED TYPE; SODIUM HYDROXIDE

Elevate Hand Sanitizer

Active Ingredient

Alcohol 62%

Purpose

Antiseptic

Uses

■ hand sanitizer to help reduce bacteria on the skin

Warnings

Flammable. Keep away from fire or flame. For external use only

When using this product

■ avoid getting into the eyes. ■ In case of eye contact immediately flush eyes thoroughly with water

Stop use and ask a doctor if

■ if irritation or redness develops ■ condition persists for more than 72 hours ■ redness is present

Keep out of reach of children

In case of accidental ingestion, contact a doctor or Poison Control Center immediately.

Directions

■ place enough product in your palm to thoroughly cover both hands ■ rub hands together until dry ■ no rinsing required

Other information

■ do not store above 105ºF ■ may discolor some fabrics or surfaces

Inactive ingredients

carbomer, deionized water, propylene glycol, sodium hydroxide